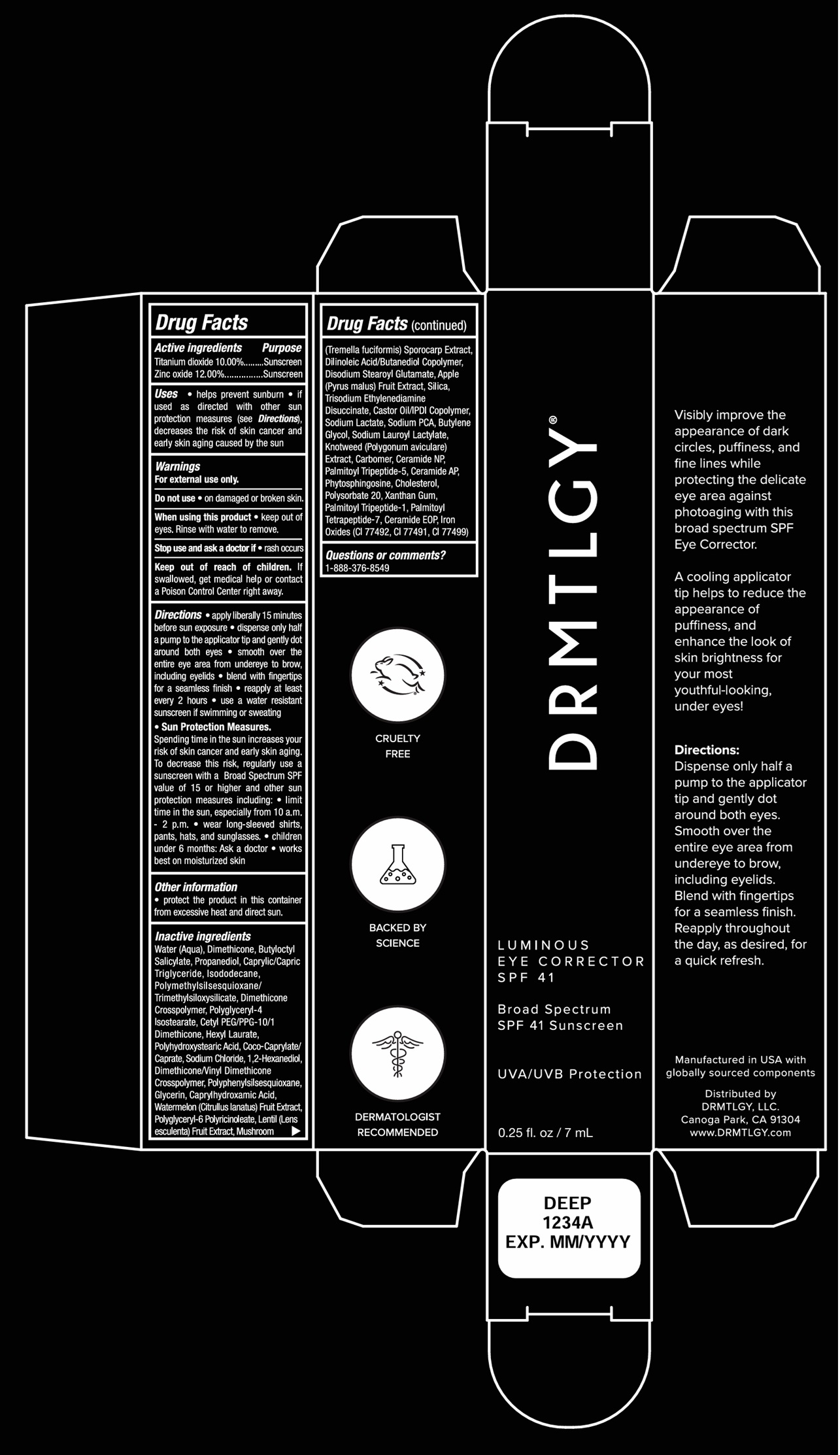 DRUG LABEL: LUMINOUS EYE CORRECTOR SPF 41 - DEEP
NDC: 83286-006 | Form: CREAM
Manufacturer: Drmtlgy, LLC
Category: otc | Type: HUMAN OTC DRUG LABEL
Date: 20251112

ACTIVE INGREDIENTS: TITANIUM DIOXIDE 10 g/100 mL; ZINC OXIDE 12 g/100 mL
INACTIVE INGREDIENTS: WATER; DIMETHICONE, UNSPECIFIED; BUTYLOCTYL SALICYLATE; PROPANEDIOL; MEDIUM-CHAIN TRIGLYCERIDES; ISODODECANE; POLYMETHYLSILSESQUIOXANE/TRIMETHYLSILOXYSILICATE; DIMETHICONE CROSSPOLYMER (450000 MPA.S); POLYGLYCERYL-4 ISOSTEARATE; CETYL PEG/PPG-10/1 DIMETHICONE (HLB 5); HEXYL LAURATE; POLYHYDROXYSTEARIC ACID (2300 MW); COCOYL CAPRYLOCAPRATE; SODIUM CHLORIDE; 1,2-HEXANEDIOL; DIMETHICONE/VINYL DIMETHICONE CROSSPOLYMER (SOFT PARTICLE); PHENYLSILANETRIOL; GLYCERIN; CAPRYLHYDROXAMIC ACID; WATERMELON; POLYGLYCERYL-6 POLYRICINOLEATE; VICIA LENS FRUIT; TREMELLA FUCIFORMIS FRUITING BODY; DILINOLEIC ACID/BUTANEDIOL COPOLYMER; DISODIUM STEAROYL GLUTAMATE; APPLE; SILICON DIOXIDE; TRISODIUM ETHYLENEDIAMINE DISUCCINATE; CASTOR OIL/IPDI COPOLYMER; SODIUM LACTATE; SODIUM PYRROLIDONE CARBOXYLATE; BUTYLENE GLYCOL; SODIUM LAUROYL LACTYLATE; POLYGONUM AVICULARE TOP; CARBOMER HOMOPOLYMER, UNSPECIFIED TYPE; CERAMIDE NP; PALMITOYL TRIPEPTIDE-5; CERAMIDE AP; PHYTOSPHINGOSINE; CHOLESTEROL; POLYSORBATE 20; XANTHAN GUM; PALMITOYL TRIPEPTIDE-1; PALMITOYL TETRAPEPTIDE-7; CERAMIDE 1; FERRIC OXIDE YELLOW; FERRIC OXIDE RED; FERROSOFERRIC OXIDE

DRMTLGY® LUMINOUS EYE CORRECTOR SPF 41

Active ingredients

Titanium dioxide 10.00%
Zinc oxide 12.00%

Purpose

Sunscreen

Uses

• helps prevent sunburn • if used as directed with other sun protection measures (see Directions), decreases the risk of skin cancer and early skin aging caused by the sun

Warnings

For external use only.

Do not use • on damaged or broken skin.

When using this product • keep out of eyes. Rinse with water to remove.

Stop use and ask a doctor if • rash occurs

Keep out of reach of children. If swallowed, get medical help or contact a Poison Control Center right away.

Directions

• apply liberally 15 minutes before sun exposure • dispense only half a pump to the applicator tip and gently dot around both eyes • smooth over the entire eye area from undereye to brow, including eyelids • blend with fingertips for a seamless finish • reapply at least every 2 hours • use a water resistant sunscreen if swimming or sweating
• Sun Protection Measures.
Spending time in the sun increases your risk of skin cancer and early skin aging. To decrease this risk, regularly use a sunscreen with a Broad Spectrum SPF value of 15 or higher and other sun protection measures including: • limit time in the sun, especially from 10 a.m. - 2 p.m. • wear long-sleeved shirts, pants, hats, and sunglasses. • children under 6 months: Ask a doctor • works best on moisturized skin

Other information

• protect the product in this container from excessive heat and direct sun.

Inactive ingredients

Water (Aqua), Dimethicone, Butyloctyl Salicylate, Propanediol, Caprylic/Capric Triglyceride, Isododecane, Polymethylsilsesquioxane/ Trimethylsiloxysilicate, Dimethicone Crosspolymer, Polyglyceryl-4 Isostearate, Cetyl PEG/PPG-10/1 Dimethicone, Hexyl Laurate, Polyhydroxystearic Acid, Coco-Caprylate/Caprate, Sodium Chloride, 1,2-Hexanediol, Dimethicone/Vinyl Dimethicone Crosspolymer, Polyphenylsilsesquioxane, Glycerin, Caprylhydroxamic Acid, Watermelon (Citrullus lanatus) Fruit Extract, Polyglyceryl-6 Polyricinoleate, Lentil (Lens esculenta) Fruit Extract, Mushroom (Tremella fuciformis) Sporocarp Extract, Dilinoleic Acid/Butanediol Copolymer, Disodium Stearoyl Glutamate, Apple (Pyrus malus) Fruit Extract, Silica, Trisodium Ethylenediamine Disuccinate, Castor Oil/IPDI Copolymer, Sodium Lactate, Sodium PCA, Butylene Glycol, Sodium Lauroyl Lactylate, Knotweed (Polygonum aviculare) Extract, Carbomer, Ceramide NP, Palmitoyl Tripeptide-5, Ceramide AP, Phytosphingosine, Cholesterol, Polysorbate 20, Xanthan Gum, Palmitoyl Tripeptide-1, Palmitoyl Tetrapeptide-7, Ceramide EOP, Iron Oxides (CI 77492, CI 77491, CI 77499)

Questions or comments?

1-888-376-8549

Broad Spectrum SPF 41 Sunscreen

UVA/UVB Protection

Visibly improve the appearance of dark circles, puffiness, and fine lines while protecting the delicate eye area against photoaging with this broad spectrum SPF Eye Corrector.

A cooling applicator tip helps to reduce the appearance of puffiness, and enhance the look of skin brightness for your most youthful-looking, under eyes!

Directions:
Dispense only half a pump to the applicator tip and gently dot around both eyes. Smooth over the entire eye area from undereye to brow, including eyelids. Blend with fingertips for a seamless finish. Reapply throughout the day, as desired, for a quick refresh.

Manufactured in USA with globally sourced components

Distributed by:
DRMTLGY, LLC.
Canoga Park, CA 91304
www.DRMTLGY.com

CRUELTY FREE

BACKED BY SCIENCE

DERMATOLOGIST RECOMMENDED